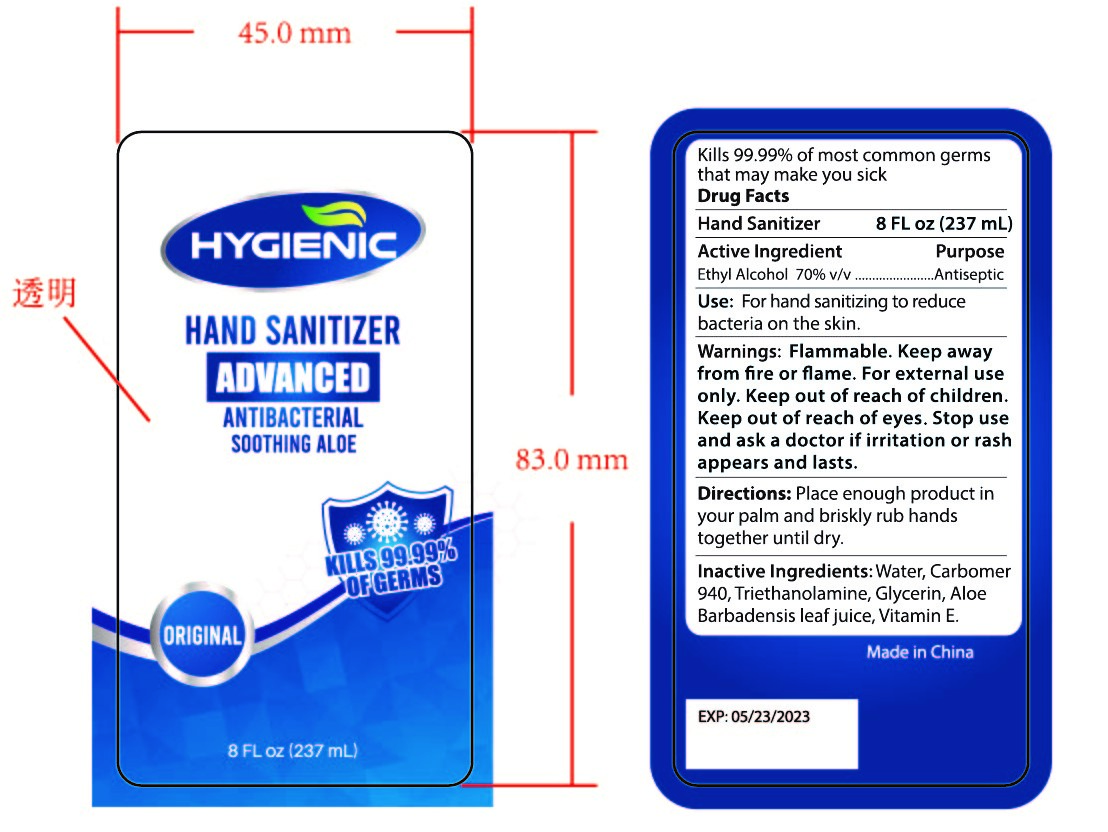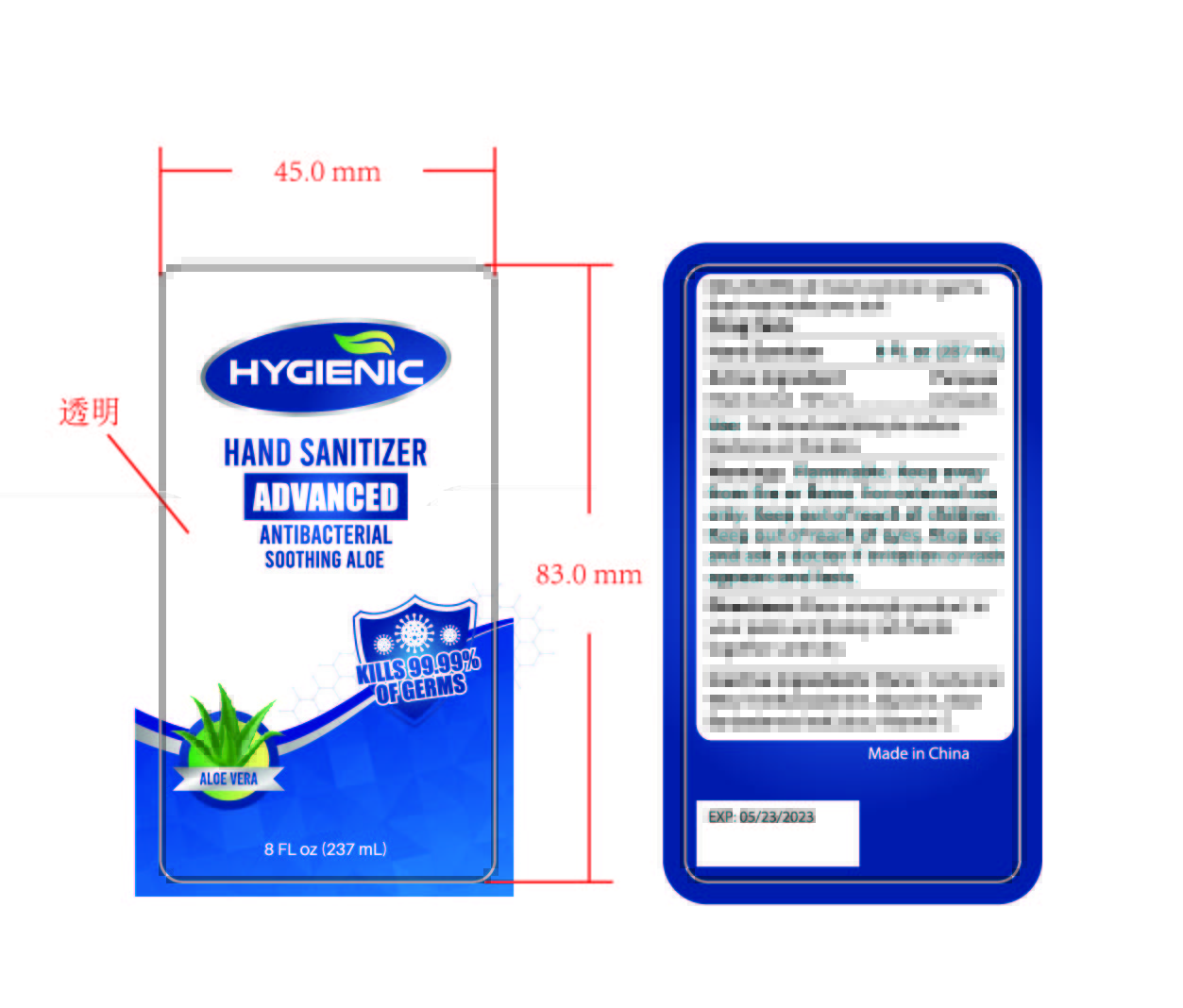 DRUG LABEL: HAND SANITIZER
NDC: 47993-245 | Form: GEL
Manufacturer: NINGBO JIANGBEI OCEAN STAR TRADING CO.,LTD
Category: otc | Type: HUMAN OTC DRUG LABEL
Date: 20201104

ACTIVE INGREDIENTS: ALCOHOL 70 mL/100 mL
INACTIVE INGREDIENTS: WATER; ALOE VERA LEAF; GLYCERIN; TRIETHANOLAMINE BENZOATE; TOCOPHEROL; CARBOMER 940

47993-245

Active ingredients

Ethyl Alcohol 70%（V/V）

PURPOSE

Antiseptic

Warnings:

Flammable. Keep away from fire or flame. For external use only. Keep out of reach of children. Keep out of reach of eyes.

Keep out of reach of children.

Stop use and ask a doctor if irritation or rash appears and lasts.

Uses：

For hand sanitizing to reduce bacteria on the skin.

Directions:

Place enough product in your palm and briskly rub hands together until dry.

Inactive Ingredients:

Water,Carbomer 940,Triethanolamine,Glycerin,Aloe Barbadensis Leaf Juice,Vitamin E